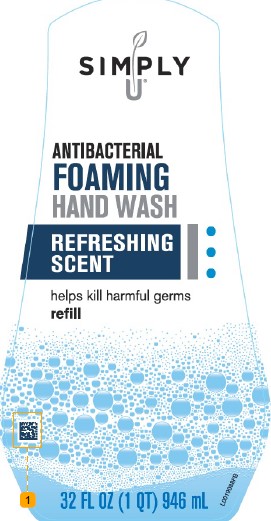 DRUG LABEL: Benzalkonium chloride
NDC: 11344-628 | Form: LIQUID
Manufacturer: Consumer Product Partners, LLC
Category: otc | Type: HUMAN OTC DRUG LABEL
Date: 20250214

ACTIVE INGREDIENTS: BENZALKONIUM CHLORIDE 1.3 mg/1 mL
INACTIVE INGREDIENTS: WATER; COCAMIDOPROPYL BETAINE; LAURAMIDOPROPYLAMINE OXIDE; LAURAMINE OXIDE; MYRISTAMIDOPROPYLAMINE OXIDE; GLYCERIN; CITRIC ACID MONOHYDRATE; EDETATE SODIUM; SULISOBENZONE; SODIUM BENZOATE; FD&C BLUE NO. 1; D&C RED NO. 33

Simply U 628.002/628AD-AF
Antibacterial Foaming Hand Wash

Active ingredient

Benzalkonium chloride 0.13%

Purpose

Antibacterial

Use

for handwashing to decrease bacteria on the skin

Warnings

For external use only: hands only

When using this product

- avoid contact with eyes. If contact occurs, rinse eyes with water.

Stop use and ask a doctor if

- irritation or redness develops
- condition persists for more than 72 hours

Keep out of reach of children.

if swallowed, get medical help or contact a Poison Control Center right away.

Directions

- wet hands
- apply palmful to dry hands
- scrub thoroughly
- rinse thoroughly

Inactive ingredients

water, cocamidopropyl betaine, lauramidopropylamine oxide, lauramine oxide, myristamidopropylamine oxide, glycerin, fragrance, citric acid, tetrasodium EDTA, benzophenone-4, sodium benzoate, blue 1, red 33

Questions?

1-888-593-0593

Adverse reactions

Distributed by:

Consumer Product Partners, LLC

St. Louis, MO 63114

Principal panel display

SIMPLY U

ANTIBACTERIAL

FOAMING

HAND WASH

REFRESHING SCENT

helps kill harmful germs

refill

32 FL OZ (1 QT) 946 mL